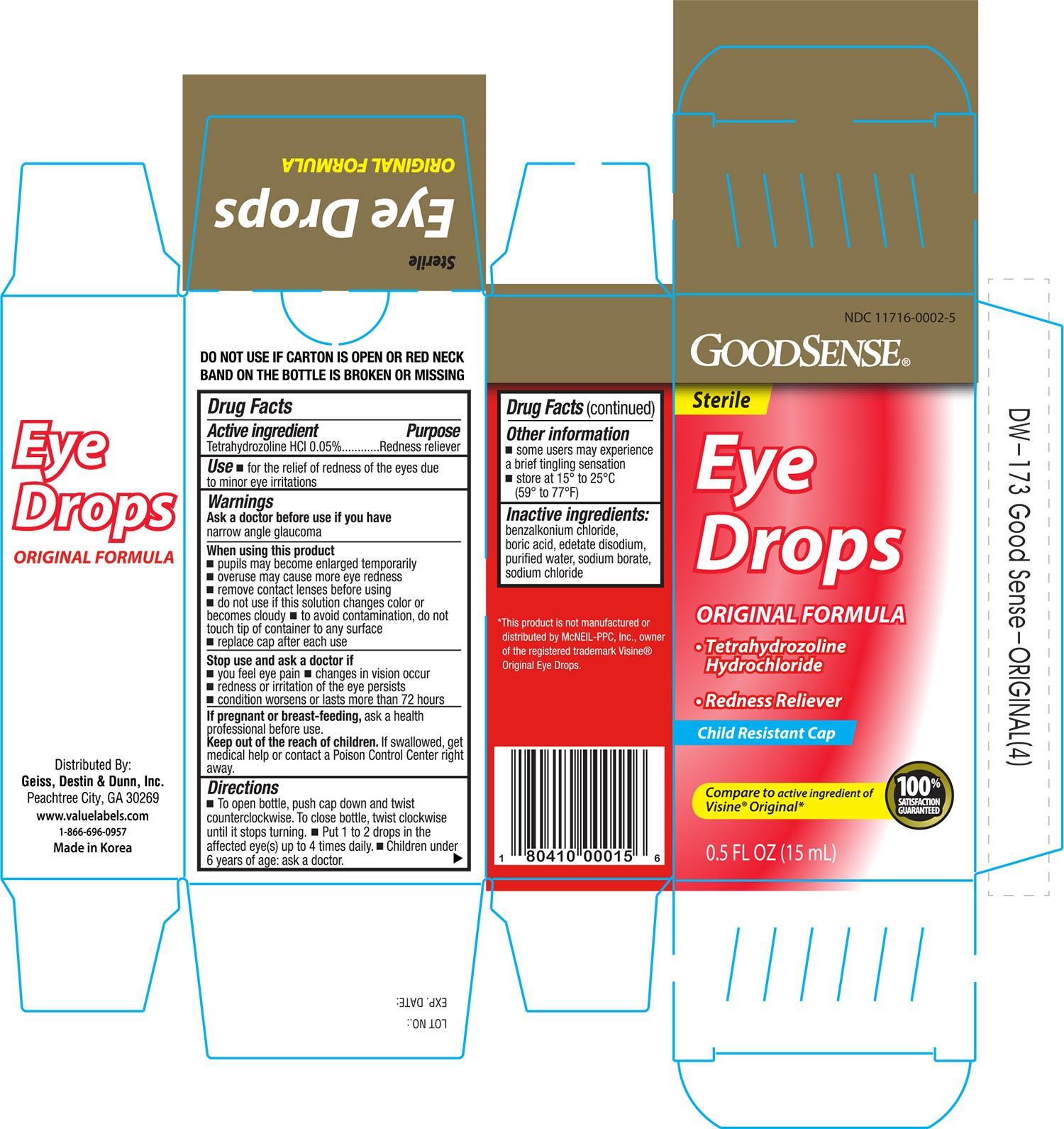 DRUG LABEL: GOODSENSE ORIGINAL EYE DROPS
NDC: 11716-0002 | Form: SOLUTION
Manufacturer: HANLIM PHARM. CO., LTD.
Category: otc | Type: HUMAN OTC DRUG LABEL
Date: 20141126

ACTIVE INGREDIENTS: TETRAHYDROZOLINE HYDROCHLORIDE 0.5 mg/1 mL
INACTIVE INGREDIENTS: BENZALKONIUM CHLORIDE; BORIC ACID; EDETATE DISODIUM; WATER; SODIUM CHLORIDE; SODIUM BORATE

Active ingredient Purpose

Tetrahydrozoline HCL 0.05%................................Redness Reliever

Uses

- for the relief of redness of the eyes due to minor eye irritations

Warnings

Ask a doctor before use if you have narrow angle glaucoma

When using this product

- pupils may become enlarged temporarily
- overuse may cause more eye redness
- remove contact lenses before using
- do not use if this solution changes color or becomes cloudy
- to avoid contamination, do not touch tip of container to any surface
- replace cap after each use

Stop use and ask a doctor if

- you feel eye pain
- changes in vision occur
- redness or irritation of the eye lasts
- condition worsens or lasts more than 72 hours

PREGNANCY OR BREAST FEEDING

If pregnant or breast-feeding, ask a health professional before use.

Keep out of the reach of children.

If swallowed, get medical help or contact a Poison Control Center right away.

Directions

- To open bottle, push cap down and twist counter-clockwise. To close bottle, twist clockwise until it stops turning.
- put 1 to 2 drops in the affected eye(s) up to 4 times daily
- children under 6 years of age: ask a doctor

Other information

- some users may experience a brief tingling sensation
- store at 15o to 25oC (59o to 77oF)

DOSAGE AND ADMINISTRATION

Distributed by:

Geiss, Destin & Dunn, Inc.

Peachtree City, GA 30269

Made in Korea

INACTIVE INGREDIENT

Inactive ingredients: benzalkonium chloride, boric acid, edetate disodium, purified water, sodium chloride, and sodium borate